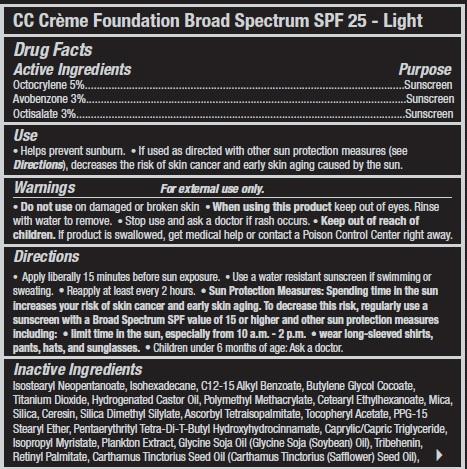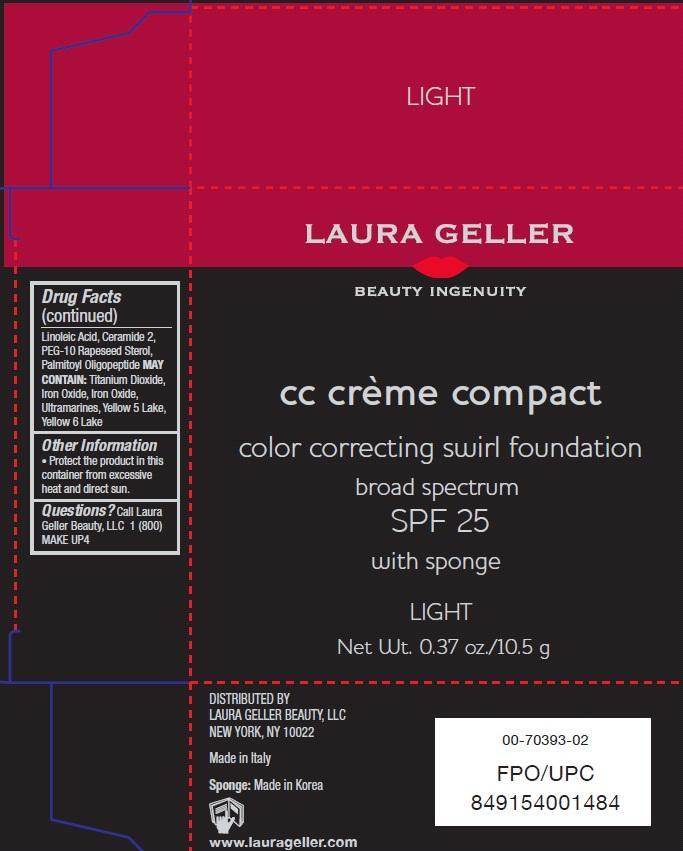 DRUG LABEL: color correcting swirl foundation broad spectrum SPF 25
NDC: 51389-119 | Form: CREAM
Manufacturer: LAURA GELLER MAKE UP INC.
Category: otc | Type: HUMAN OTC DRUG LABEL
Date: 20130502

ACTIVE INGREDIENTS: OCTOCRYLENE 5 g/100 g; AVOBENZONE 3 g/100 g; OCTISALATE 3 g/100 g
INACTIVE INGREDIENTS: ISOSTEARYL NEOPENTANOATE; ISOHEXADECANE; TITANIUM DIOXIDE; CETEARYL ETHYLHEXANOATE; MICA; SILICON DIOXIDE; CERESIN; SILICA DIMETHYL SILYLATE; ASCORBYL TETRAISOPALMITATE; .ALPHA.-TOCOPHEROL ACETATE; PENTAERYTHRITOL TETRAKIS(3-(3,5-DI-TERT-BUTYL-4-HYDROXYPHENYL)PROPIONATE); TRICAPRIN; ISOPROPYL MYRISTATE; SOYBEAN OIL; TRIBEHENIN; VITAMIN A PALMITATE; SAFFLOWER OIL; LINOLEIC ACID; CERAMIDE 2; RAPESEED STEROL; PALMITOYL OLIGOPEPTIDE; FERRIC OXIDE RED; FD&C YELLOW NO. 5; FD&C YELLOW NO. 6

Drug Facts

Active Ingredients

Octocrylene 5%

Avobenzone 3%

Octisalate 3%

Purpose

Sunscreen

Use

- Helps prevent sunburn.
- If used as directed with other sun protection measures (see Directions),decreases the risk of skin cancer and early skin aging caused by the sun.

Warnings

For external use only.

Do not use on damaged or broken skin.

When using this product

Keep out of eyes. Rinse with water to remove.

Stop use and ask a doctor

if rash occurs.

Keep out of reach of children.

If product is swallowed, get medical help or contact a Poison Control Center right away.

Directions

- Apply generously 15 minutes before sun exposure.
- Use a water resistant sunscreen if swimming or sweating.
- Reapply at least every 2 hours.
- Sun protection measures. Spending time in the sun increases your risk of skin cancer and early skin aging. To decrease this risk, regularly use a sunscreen with a broad spectrum SPF value of 15 or higher and other sun protection measures including:
-
  - limit time in the sun, especially from 10 a.m.- 2 p.m.
  - wear long-sleeved shirts, pants, hats and sunglasses
- Children under 6 months of age: Ask a doctor.

Other Information

- Protect the product in this container from excessive heat and direct sun.

Inactive Ingredients

Isostearyl Neopentanoate, Isohexadecane, C12-15 Alkyl Benzoate, Butylene Glycol Cocoate, Titanium Dioxide, Hydrogenated Castor Oil, Polymethyl Methacrylate, Cetearyl Ethylhexanoate, Mica, Silica, Ceresin, Silica Dimethyl Silylate, Ascorbyl Tetraisopalmitate, Tocopheryl Acetate, PPG-15 Stearyl Ether, Pentaerythrityl Tetra-Di-T-Butyl Hydroxyhydrocinnamate, Caprylic/Capric Triglyceride, Isopropyl Myristate, Plankton Extract, Glycine Soja Oil (Glycine Soja (Soybean) Oil), Tribehenin, Retinyl Palmitate, Carthamus Tinctorius Seed Oil (Carthamus Tinctorius (Safflower) Seed Oil),Linoleic Acid, Ceramide 2, PEG-10 Rapeseed Sterol, Palmitoyl Oligopeptide

MAY CONTAIN: Titanium Dioxide, Iron Oxide, Iron Oxide, Ultramarines, Yellow 5 Lake, Yellow 6 Lake

Questions?

Call Laura Geller Beauty, LLC., 1(800) MAKE UP4

Principal Display Panel

LAURA GELLER

BEAUTY INGENUITY

cc creme compact

color correcting swirl foundation

braod spectrum

SPF 25

with sponge

LIGHT

Net Wt. 0.37 oz/10.5 g